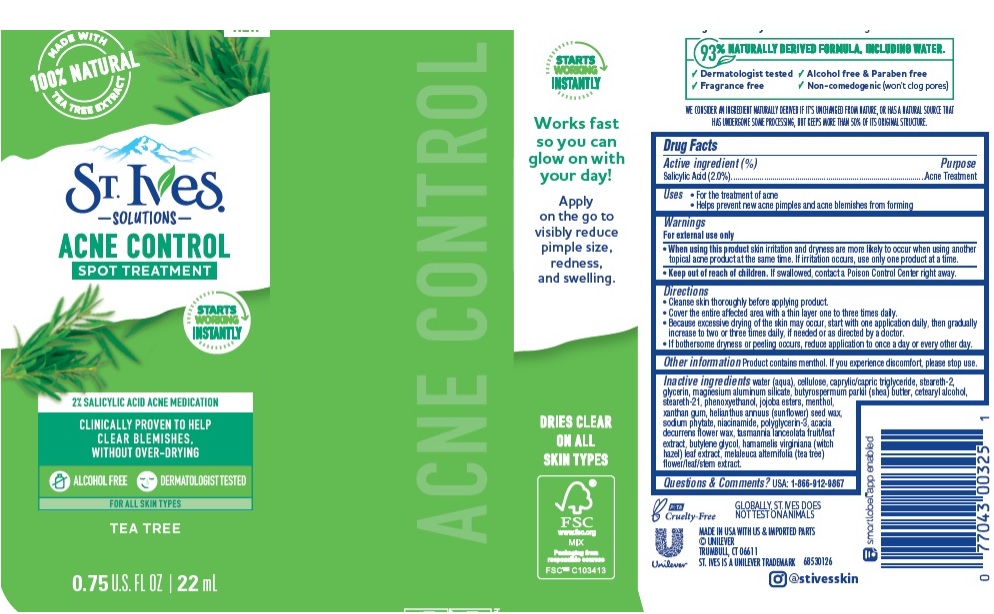 DRUG LABEL: St. Ives
NDC: 64942-1861 | Form: LOTION
Manufacturer: CONOPCO Inc. d/b/a Unilever
Category: otc | Type: HUMAN OTC DRUG LABEL
Date: 20241107

ACTIVE INGREDIENTS: SALICYLIC ACID 0.02 g/1 g
INACTIVE INGREDIENTS: WATER; GLYCERIN; MEDIUM-CHAIN TRIGLYCERIDES; STEARETH-2; MAGNESIUM ALUMINUM SILICATE; SHEA BUTTER; STEARETH-21; CETOSTEARYL ALCOHOL; PHENOXYETHANOL; HYDROGENATED JOJOBA OIL, RANDOMIZED; MENTHOL; XANTHAN GUM; HELIANTHUS ANNUUS SEED WAX; PHYTATE SODIUM; NIACINAMIDE; POLYGLYCERIN-3; ACACIA DECURRENS FLOWER WAX; BUTYLENE GLYCOL; MELALEUCA ALTERNIFOLIA FLOWERING TOP; HAMAMELIS VIRGINIANA LEAF; POWDERED CELLULOSE

St. Ives Solutions Acne Control Spot Treatment

Active ingredient

Salicylic Acid (2%)

Purpose

Acne Treatment

Uses

For the mangement of acne
Helps prevent new acne pimples and acne blemishes from forming

Warnings

For external use only
When using this product skin irritation and dryness is more likely to occur if you use another topical acne medication at the same time. If irritation occues, only use one topical acne medication at a time.

Keep out of reach of children
If swallowed, get medical help or contact a Poison Control Center right away.

Directions

Cleanse skin thoroughly before applying product
Cover the entire affected area with a thin layer one to three times daily
Because excessive drying of the skin may occur, start with one application daily, then gradually increase to two or three times daily, if needed or as directed by a doctor.
If bothersome dryness or peeling occurs, reduce application to once a day or every other day.

Other information

Product contains menthol. If you experience discomfort, please stop use

Inactive ingredients

Water (Aqua), Cellulose, Caprylic/Capric Triglyceride, Steareth-2, Glycerin, Magnesium Aluminum Silicate, Butyrospermum Parkii (Shea) Butter, Cetearyl Alcohol, Steareth-21, Phenoxyethanol, Jojoba Esters, Menthol, Xanthan Gum, Helianthus Annuus (Sunflower) Seed Wax, Sodium Phytate, Niacinamide, Polyglycerin-3, Acacia Decurrens Flower Wax, Tasmannia Lanceolata Fruit/Leaf Extract, Butylene Glycol, Hamamelis Virginiana (Witch Hazel) Leaf Extract, Melaleuca Alternifolia (Tea Tree) Flower/Leaf/Stem Extract.

Questions or comments?

USA: 1-800-912-9867